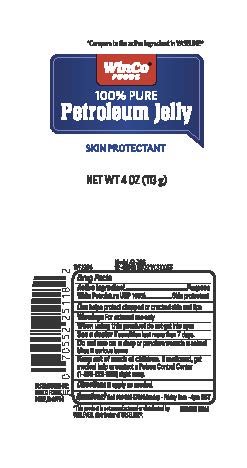 DRUG LABEL: WinCo FoodsPetroleum Jelly
NDC: 67091-412 | Form: JELLY
Manufacturer: WinCo Foods, LLC
Category: otc | Type: HUMAN OTC DRUG LABEL
Date: 20251228

ACTIVE INGREDIENTS: PETROLATUM 100 g/100 g

WinCo Foods Petroleum Jelly

Drug Facts

Active Ingredient

White Petrolatum USP 100%

Purpose

Skin protectant

Uses

temporarily protects ■ minor cuts, scrapes,
burns ■ and help relieve chapped or cracked
skin and lips ■ from the drying effects of wind and
cold weather

Directions

apply as needed

INACTIVE INGREDIENT

Water

Warning

For external use only

Keep out of reach of children

if swallowed, get medical help or contact a Poison Control Center (1-800-222-1222) right away